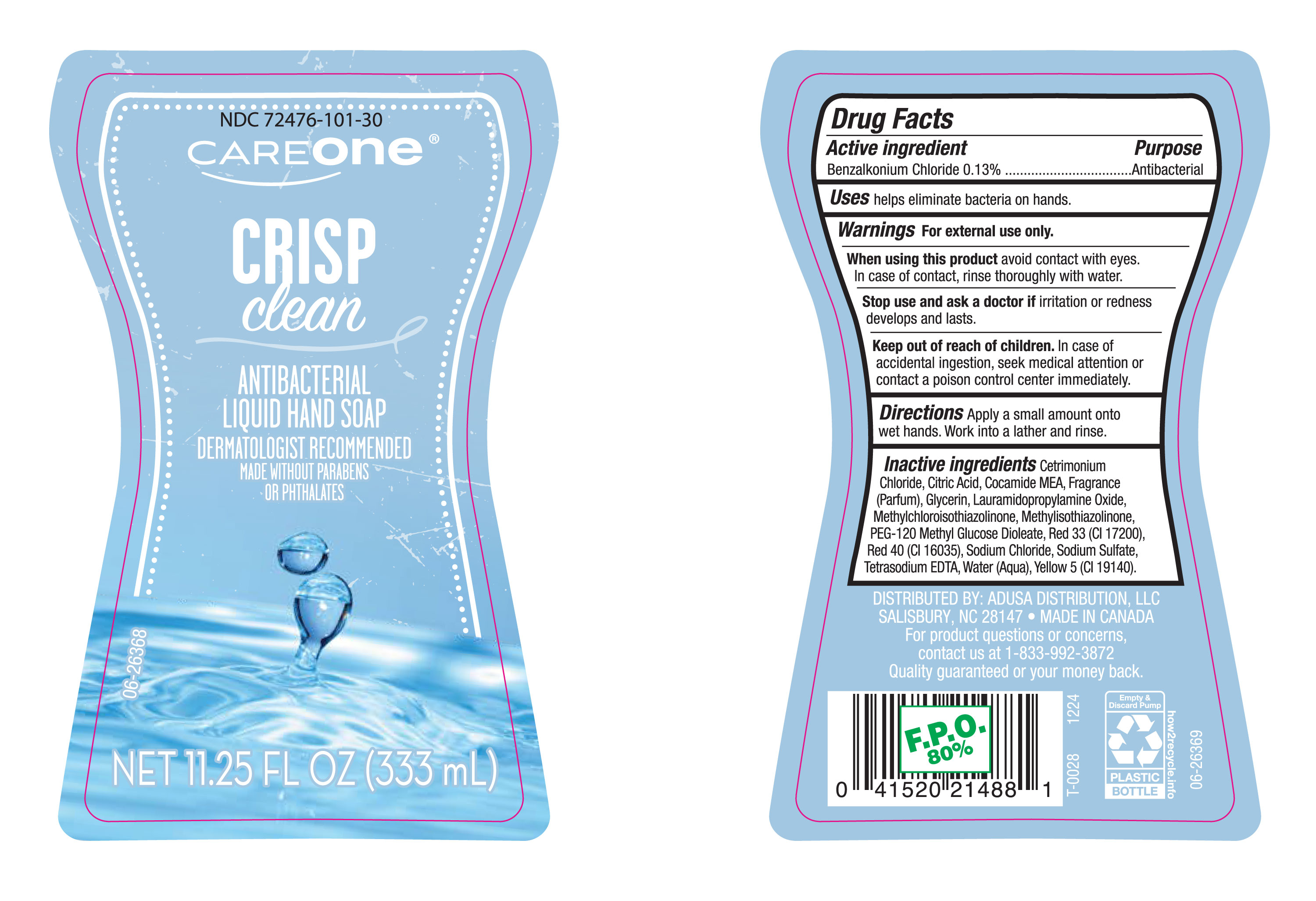 DRUG LABEL: Care One Crisp Clean
NDC: 72476-101 | Form: LIQUID
Manufacturer: RETAIL BUSINESS SERVICES , LLC
Category: otc | Type: HUMAN OTC DRUG LABEL
Date: 20250116

ACTIVE INGREDIENTS: BENZALKONIUM CHLORIDE 130 mg/100 mL
INACTIVE INGREDIENTS: YELLOW 5; FRAGRANCE CLEAN ORC0600327; CITRIC ACID; GLYCERIN; SODIUM CHLORIDE; SODIUM SULFATE; TETRASODIUM EDTA; WATER; COCAMIDE MEA; METHYLISOTHIAZOLINONE; PEG-120 METHYL GLUCOSE DIOLEATE; RED 33; METHYLCHLOROISOTHIAZOLINONE; CETRIMONIUM CHLORIDE; LAURAMIDOPROPYLAMINE OXIDE; RED 40

NDC-72476-101, Careone Crisp Clean Antibacterial Liquid Hand Soap.

Active Ingredient

Benzalkonium Chloride 0.13%

Purpose

Antibacterial

Uses

Helps eliminate bacteria on hands

Warnings

For external use only

When using the product

Avoid contact with eyes. In case of contact, rinse thoroughly with water.

Stop use andask a doctor if

irritation or redness develops and lasts.

Keep out of reach of children.

In case of accidental ingestion, seek medical attention or contact a poison control center immediately.

Directions

Apply a small amont onto wet hands. Work into a lather and rinse.

Inactive Ingredients

Centrimonium Chloride, Citric Acid, Cocamide MEA, Fragrance (Parfum), Glycerin, Lauramidopropylamine Oxide, Methylchloroisothiazolinone, Methylisothiazolinone, PEG-120 Methyl Glucose Dioleate, Red 33 (CI 17200), Red 40 (CI 16035), Sodium Chloride, Sodium Sulfate, Tetrasodium EDTA, Water (Aqua), Yellow (CI 19140)